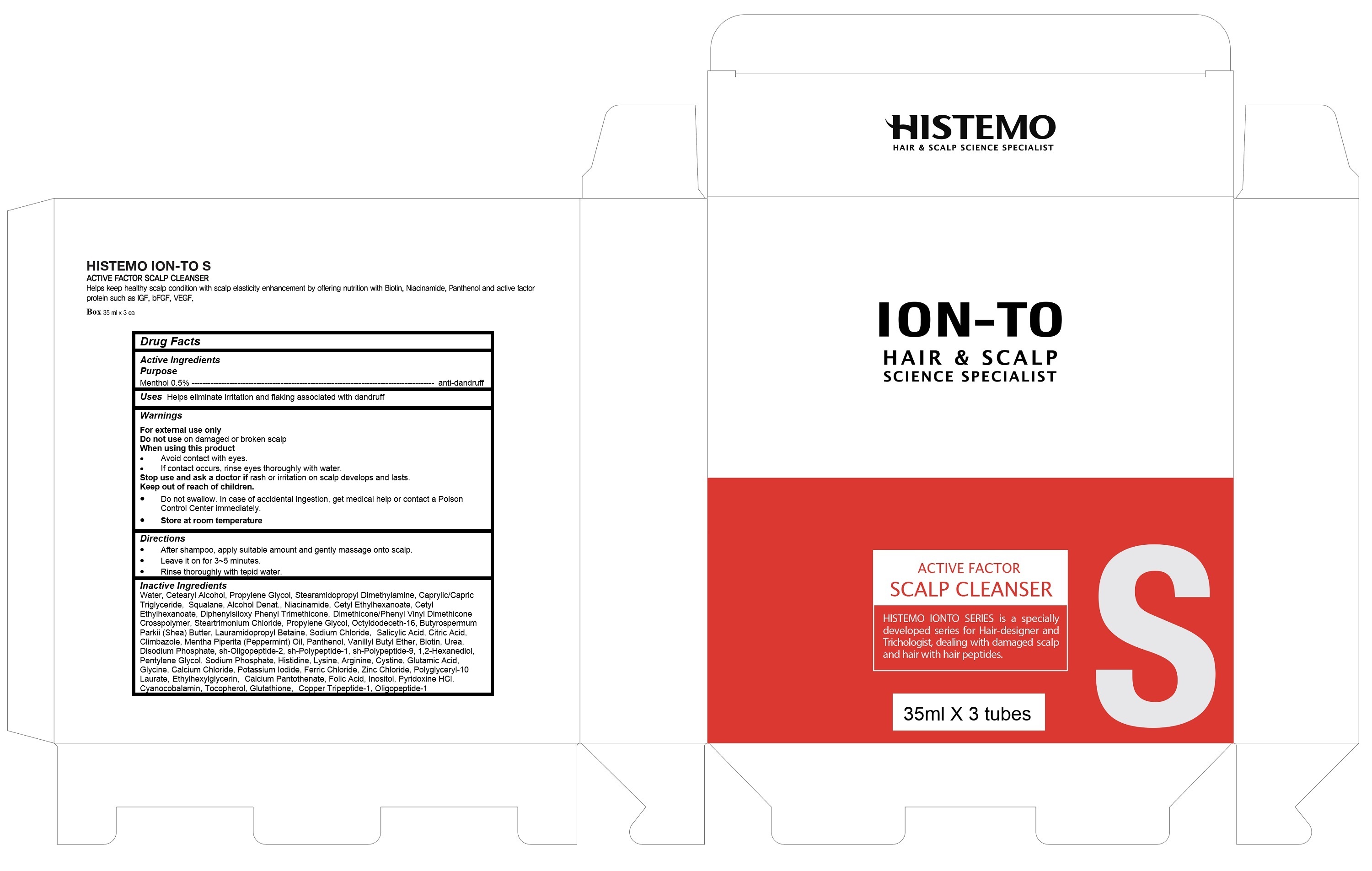 DRUG LABEL: ION-TO SCALP CLEANSER S
NDC: 72978-103 | Form: CREAM
Manufacturer: HUSAZOMO USA
Category: otc | Type: HUMAN OTC DRUG LABEL
Date: 20190808

ACTIVE INGREDIENTS: MENTHOL 0.525 g/105 g
INACTIVE INGREDIENTS: PANTHENOL; WATER

ION-TO SCALP CLEANSER S

Active Ingredients

Menthol 0.5%

Purpose

Anti-dandruff

Keep out of reach of children

Do not swallow. In case of accidental ingestion, get medical help or contact a Poison Control Center immediately.

Uses

Helps eliminate irritation and flaking associated with dandruff

Warnings

For external use only

Do not use on damaged or broken scalp

When using this product

Avoid contact with eyes.
If contact occurs, rinse eyes thoroughly with water.

Stop use and ask a doctor if rash or irritation on scalp develops and lasts.

Directions

After shampoo, apply suitable amount and gently massage onto scalp.
Leave it on for 3~5 minutes.

Rinse thoroughly with tepid water.

Inactive Ingredients

Water, Cetearyl Alcohol, Propylene Glycol, Stearamidopropyl Dimethylamine, Caprylic/Capric Triglyceride, Squalane, Alcohol Denat., Niacinamide, Cetyl Ethylhexanoate, Cetyl Ethylhexanoate, Diphenylsiloxy Phenyl Trimethicone, Dimethicone/Phenyl Vinyl Dimethicone Crosspolymer, Steartrimonium Chloride, Propylene Glycol, Octyldodeceth-16, Butyrospermum Parkii (Shea) Butter, Lauramidopropyl Betaine, Sodium Chloride, Salicylic Acid, Citric Acid, Climbazole, Mentha Piperita (Peppermint) Oil, Panthenol, Vanillyl Butyl Ether, Biotin, Urea, Disodium Phosphate, sh-Oligopeptide-2, sh-Polypeptide-1, sh-Polypeptide-9, 1,2-Hexanediol, Pentylene Glycol, Sodium Phosphate, Histidine, Lysine, Arginine, Cystine, Glutamic Acid, Glycine, Calcium Chloride, Potassium Iodide, Ferric Chloride, Zinc Chloride, Polyglyceryl-10 Laurate, Ethylhexylglycerin, Calcium Pantothenate, Folic Acid, Inositol, Pyridoxine HCl, Cyanocobalamin, Tocopherol, Glutathione, Copper Tripeptide-1, Oligopeptide-1